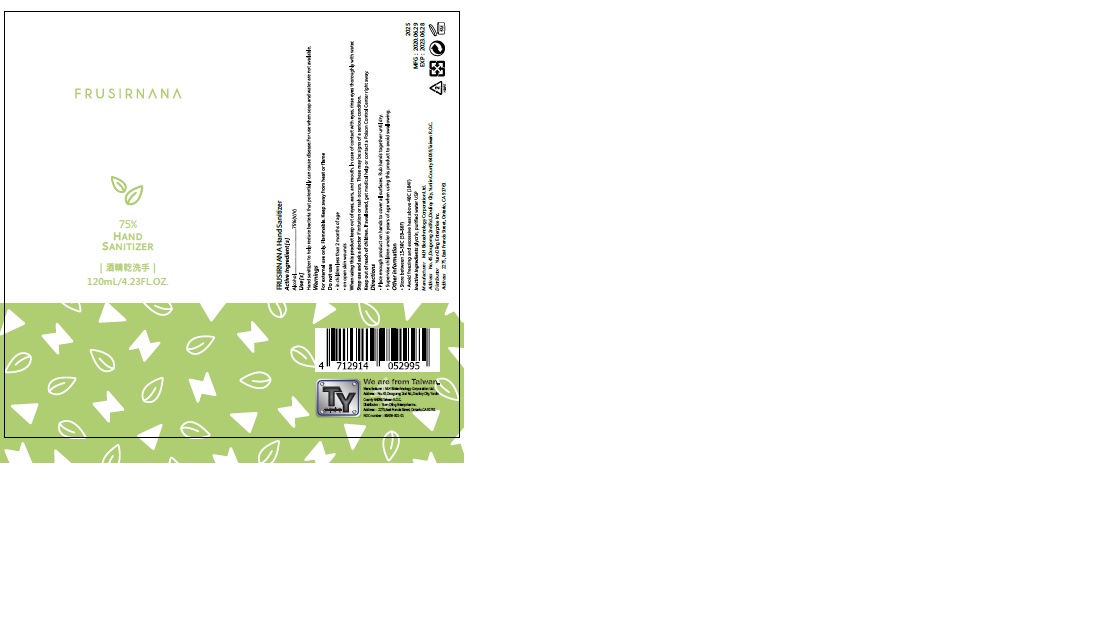 DRUG LABEL: FRUSIRNANA HAND SANITIZER
NDC: 79105-001 | Form: SOLUTION
Manufacturer: Yuen Diing Enterprise Inc.
Category: otc | Type: HUMAN OTC DRUG LABEL
Date: 20200910

ACTIVE INGREDIENTS: ALCOHOL 94.8 mL/120 mL
INACTIVE INGREDIENTS: GLYCERIN 3.6 mL/120 mL; WATER 20.64 mL/120 mL

This is a hand sanitizer manufactured according to the Temporary Policy for Preparation of Certain Alcohol-Based Hand Sanitizer Products During the Public Health Emergency (CoViD-19); Guidance for Industry.

The hand sanitizer is manufactured using only the follow United States Pharmacopoeia (USP) grade ingredients in the preparation of the product (percentage in final product formulation) consistent with World Health Organization (WHO) recommendations.

The firm does not add other active or inactive ingredients. Different or additional ingredients may impact the quality and potency of the product.

Active Ingredient(s)

Alcohol 75% v/v. Purpose: Antiseptic

Purpose

Antiseptic, Hand Sanitizer

Use

Hand Sanitizer to help reduce bacteria that potentially can cause disease. For use when soap and water are not available.

Warnings

For external use only. Flammable. Keep away from heat or flame

Do not use

- in children less than 2 months of age
- on open skin wounds

Directions

- Place enough product on hands to cover all surfaces. Rub hands together until dry.
- Supervise children under 6 years of age when using this product to avoid swallowing.

Other information

- Store between 15-30C (59-86F)
- Avoid freezing and excessive heat above 40C (104F)

Inactive ingredients

glycerin, purified water USP

Package Label - Principal Display Panel

FRUSIRNANA HAND SANITIZER